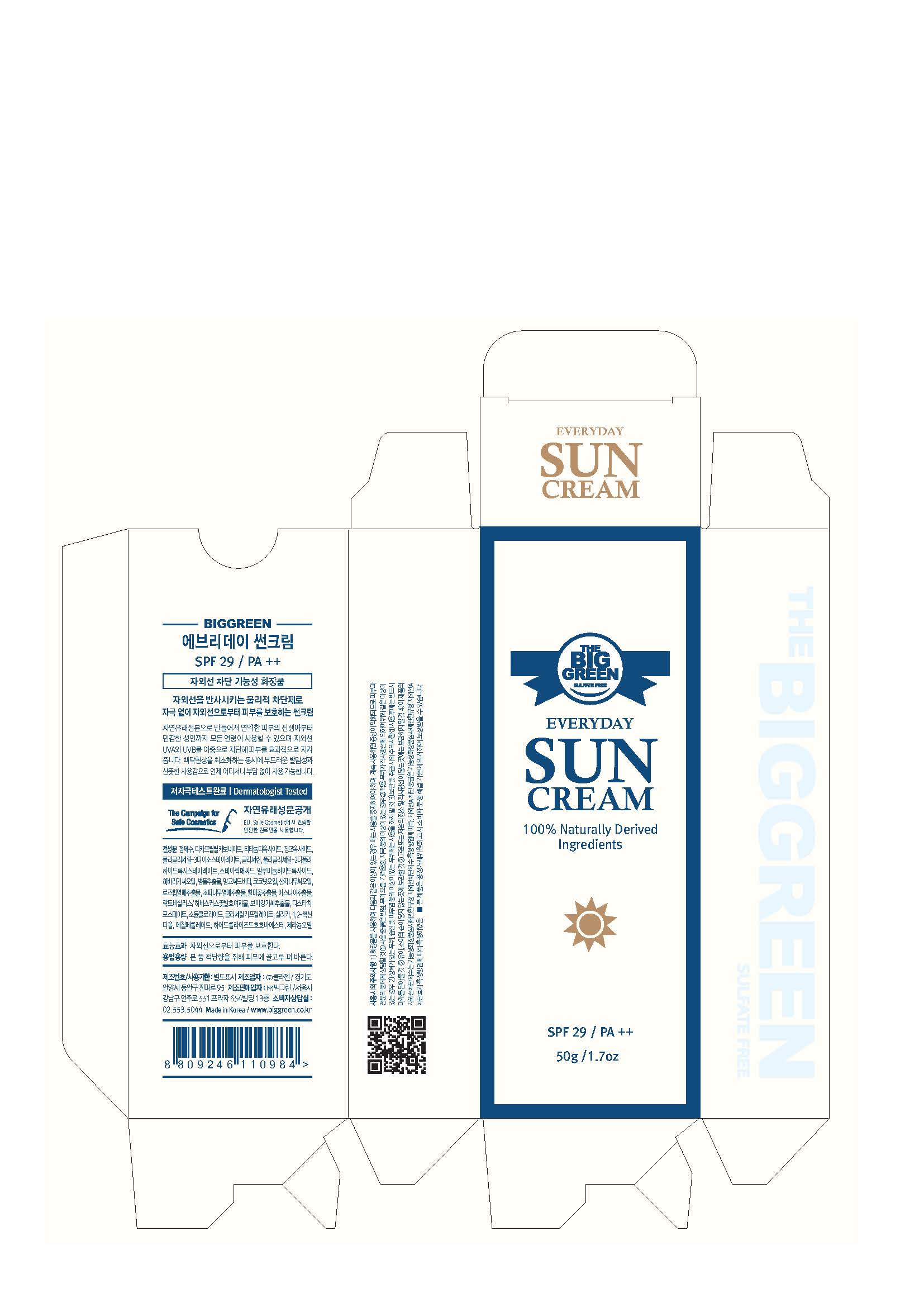 DRUG LABEL: BIGGREEN EVERYDAY SUN
NDC: 71251-0001 | Form: CREAM
Manufacturer: BIGGREEN INC.
Category: otc | Type: HUMAN OTC DRUG LABEL
Date: 20180521

ACTIVE INGREDIENTS: TITANIUM DIOXIDE 11.25 g/100 g; ZINC OXIDE 4.85 g/100 g
INACTIVE INGREDIENTS: WATER; GLYCERIN

Drug Facts

ACTIVE INGREDIENT

Titanium Dioxide, Zinc Oxide

INACTIVE INGREDIENT

Water, Dicaprylyl Carbonate, Polyglyceryl-3 Diisostearate, Glycerin, Polyglyceryl-2 Dipolyhydroxystearate, Stearic Acid, Aluminum Hydroxide, Helianthus Annuus (Sunflower) Seed Oil, Centella Asiatica Extract, Mangifera Indica (Mango) Seed Butter, Cocos Nucifera (Coconut) Oil, Hippophae Rhamnoides Seed Oil, Rosa Canina Fruit Extract, Zanthoxylum Piperitum Fruit Extract, Pulsatilla Koreana Extract, Usnea Barbata (Lichen) Extract, Lactobacillus/Hibiscus Sabdariffa FlowerFerment Filtrate, Voacanga Africana Seed Extract, Distarch Phosphate, Sodium Chloride, Glyceryl Caprylate, Silica, 1,2-Hexanediol, Ethyl Ferulate, Hydrolyzed Jojoba Esters, Geranium Maculatum Oil

PURPOSE

Skin Protectant - Sun Block

keep out or reach of the children

INDICATIONS AND USAGE

- Apply liberally 15 minutes before sun exposure.
- Children under 6 months ask a doctor.
- Reapply after water activity.

WARNINGS

1. Do not use in the following cases(Eczema and scalp wounds)
2.Side Effects
1)Due to the use of this druf if rash, irritation, itching and symptopms of hypersnesitivity occur dicontinue use and consult your phamacisr or doctor
3.General Precautions
1)If in contact with the eyes, wash out thoroughty with water If the symptoms are servere, seek medical advice immediately
2)This product is for exeternal use only. Do not use for internal use
4.Storage and handling precautions
1)If possible, avoid direct sunlight and store in cool and area of low humidity
2)In order to maintain the quality of the product and avoid misuse
3)Avoid placing the product near fire and store out in reach of children

DOSAGE AND ADMINISTRATION

for external use only